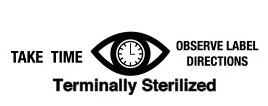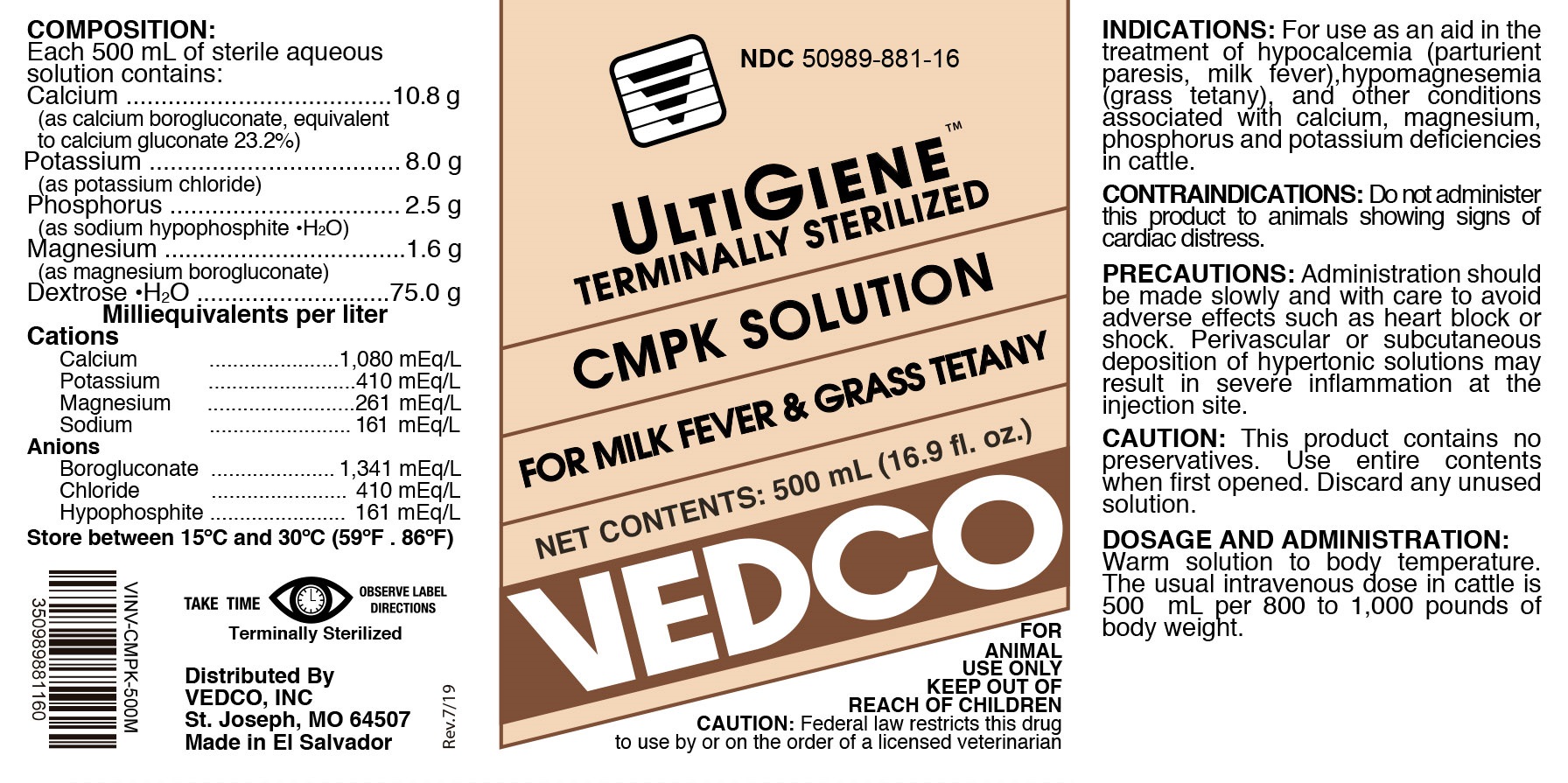 DRUG LABEL: CMPK
NDC: 50989-881 | Form: INJECTION, SOLUTION
Manufacturer: Vedco
Category: animal | Type: PRESCRIPTION ANIMAL DRUG LABEL
Date: 20190823

ACTIVE INGREDIENTS: CALCIUM 10.8 g/500 mL; POTASSIUM 8.0 g/500 mL; PHOSPHORUS 2.5 g/500 mL; MAGNESIUM 1.6 g/500 mL; DEXTROSE MONOHYDRATE 75.0 g/500 mL

CMPK SOLUTION

COMPOSITION

Each 500 mL of sterile aqueous contains:

Calcium....................... 10.8 g
(as calcium borogluconate, equivalent to calcium gluconae.... 23.2%)

Potassium............... 8.0 g
(as potassium chloride)

Phosphorus............ 2.5 g
(as sodium hypophosphite • H2O)

Magnesium............ 1.6 g

(as magnesium borogluconate)

Dextrose • H2O

Milliequivalents per liter

Cations

Calcium.................. 1,080 mEq/L

Potassium................. 410 mEq/L

Magnesium............... 261 mEq/L

Sodium..................... 161 mEq/L

Anions

Borogluconate......... 1,341 mEq/L

Chloride...................... 410 mEq/L

Hypophophite............. 161 mEq/L

INDICATIONS

For use as an aid in treatment of hypocalcemia (parturient paresis, milk fever), hypomagnesemia (grass tetany), and other conditions associated with calcium, magnesium phosphorus and potassium deficiencies in cattle

CONTRAINDICATIONS

Do not administer this product to animals showns signs of cardiac distress.

PRECAUTIONS

Administration should be made slowly and with care to avoid adverse effects such as heart block or shock. Perivascular or subcutaneous deposition of hypertonic solutions may result in severe inflammation at the injection site.

CAUTION

This product contains no preservatives. Use entire contents when first opened. Discard any unused solution

DOSAGE AND ADMINISTRATION:

Warm solution to body temperature. The usual intravenous dose in cattle is 500 mL per 800 to 1,000 pounds of body weight

STORAGE

Store at 15oC to 30oC (59oF - 86oF).

KEEP OUT OF REACH OF CHILDREN

VETERINARY INDICATIONS

FOR ANIMAL USE ONLY

CAUTION: Federal law restricts this drug to use by or on the order of a licensed veterinarian

SAFE HANDLING WARNING

TAKE TIME OBSERVE LABEL DIRECTIONS

Termnally Sterilized

Distributed By

VEDCO, INC.

St. Joseph, MO 64507

Made in El Salvador

PRINCIPAL DISPLAY PANEL

NDC 50989-881-16

ULTIGIENETM TERMINALLY STERILIZED

CMPK SOLUTION

FOR MILK FEVER & GRASS TETANY

NET CONTENTS: 500 mL (16.9 f. oz.)

VEDCO

FOR ANIMAL USE ONLY

KEEP OUT OF REACH OF CHILDREN

CAUTION: Federal law restricts this drug to use by or on the order of a licensed veterinarian